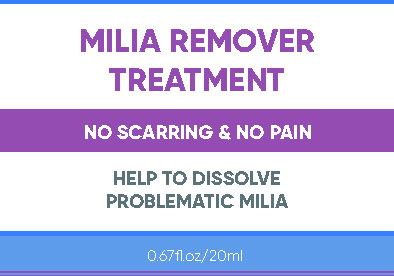 DRUG LABEL: MILIA REMOVER TREATMENT
NDC: 84023-701 | Form: LIQUID
Manufacturer: Shenzhen Yangan Technology Co., Ltd.
Category: otc | Type: HUMAN OTC DRUG LABEL
Date: 20240322

ACTIVE INGREDIENTS: DIDECYLDIMONIUM 0.025 g/100 mL
INACTIVE INGREDIENTS: AMYLOPECTIN (4,5-DIHYDROXY-1,3-DIMETHYLIMIDAZOLIDIN-2-ONE CROSS LINKED); ALPHA-TOCOPHEROL ACETATE; BENZALKONIUM; WATER; GLYCERIN; SALICYLIC ACID; XANTHAN GUM; ICODEXTRIN

MILIA REMOVER TREATMENT

MILIA REMOVER TREATMENT

ACTIVE INGREDIENT

Didecyl dimethyl ammonium chloride 0.025%

PURPOSE

Disinfectant

INDICATIONS AND USAGE

fight and reduce signs ofmilia, also help to resolveacne skin problems.

WARNINGS

For external use only.

WHEN USING

1. Cleanse your face with warm water. Dry the skin, and if possible use a facia moisturizer.
2. Drip the appropriate amount of milia remover on the milia spots and massage gently with your fingers.
3. Till the milia remover is completely absorbed, it is done and no need to remove it
4. To completely get rid of excessive skin oi and preventregrowth, Continue using for 4 weeks after the milia havebeen removed

STOP USE

Stop using and ask a doctor if rash or irritation happens.

KEEP OUT OF REACH OF CHILDREN

2. Please keep it out of reach of infants and children.

DOSAGE AND ADMINISTRATION

1. Apply daily after cleansing and toning. Twice a day for at least 4 weeks.
2.Dispense a pea-size amount of the essence on to the probmatic area and usefingertips to massage until fuily absorbed.
3. Keep using it for a period of time until the milia doesn't appear again.

STORAGE AND HANDLING

Store in a dry and cool place.

INACTIVE INGREDIENT

Water
Glycerin
Salicylic Acid
Dextrin
Xanthan Gum
Amylopectin
Tocopherol Acetate
Dodecyl Dimethyl Benzyl Ammonium Chloride 0.025% ± 10%